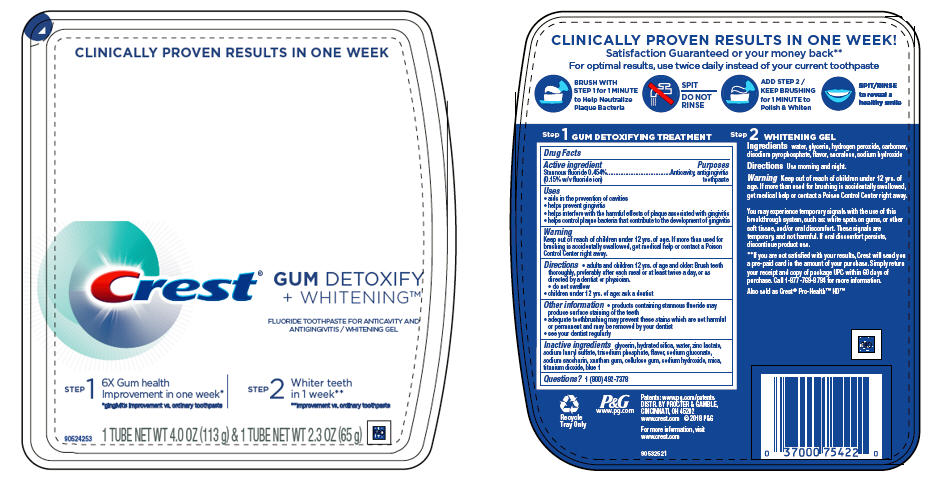 DRUG LABEL: Crest Gum Detoxify
NDC: 37000-489 | Form: KIT | Route: DENTAL
Manufacturer: The Procter & Gamble Manufacturing Company
Category: otc | Type: HUMAN OTC DRUG LABEL
Date: 20250806

ACTIVE INGREDIENTS: STANNOUS FLUORIDE 1.5 mg/1 g
INACTIVE INGREDIENTS: HYDRATED SILICA; WATER; ZINC LACTATE; SODIUM LAURYL SULFATE; SODIUM GLUCONATE; GLYCERIN; SACCHARIN SODIUM; XANTHAN GUM; CARBOXYMETHYLCELLULOSE SODIUM; SODIUM HYDROXIDE; MICA; TITANIUM DIOXIDE; FD&C BLUE NO. 1; SODIUM PHOSPHATE, TRIBASIC, ANHYDROUS

Crest® Gum Detoxify + Whitening ™

Drug Facts

Active ingredient

Stannous fluoride 0.454% (0.15% w/v fluoride ion)

Purposes

Anticavity, antigingivitis toothpaste

Uses

- aids in the prevention of cavities
- helps prevent gingivitis
- helps interfere with the harmful effects of plaque associated with gingivitis
- helps control plaque bacteria that contribute to the development of gingivitis

Warning

Keep out of reach of children under 12 yrs. of age. If more than used for brushing is accidentally swallowed, get medical help or contact a Poison Control Center right away.

Directions

- adults and children 12 yrs. of age and older: Brush teeth thoroughly, preferably after each meal or at least twice a day, or as directed by a dentist or physician.
  - do not swallow
- children under 12 yrs. of age: ask a dentist

Other information

- products containing stannous fluoride may produce surface staining of the teeth
- adequate toothbrushing may prevent these stains which are not harmful or permanent and may be removed by your dentist
- see your dentist regularly

Inactive ingredients

glycerin, hydrated silica, water, zinc lactate, sodium lauryl sulfate, trisodium phosphate, flavor, sodium gluconate, sodium saccharin, xanthan gum, cellulose gum, sodium hydroxide, polyethylene, mica, titanium dioxide, blue 1

Questions?

(800) 492-7378

Dist. by Procter & Gamble,
Cincinnati, OH 45202

PRINCIPAL DISPLAY PANEL - Kit Carton

CLINICALLY PROVEN RESULTS IN ONE WEEK

Crest®
GUM DETOXIFY

+ WHITENING™

FLUORIDE TOOTHPASTE FOR ANTICAVITY AND

ANTIGINGIVITIS/WHITENING GEL

STEP 1

6X Gum health
Improvement in one week*
*gingivitis improvement vs. ordinary toothpaste

STEP 2

Whiter teeth
in 1 week**
**improvement vs. ordinary toothpaste

1 TUBE NET WT 4.0 OZ (113 g) & 1 TUBE NET WT 2.3 OZ (65 g)